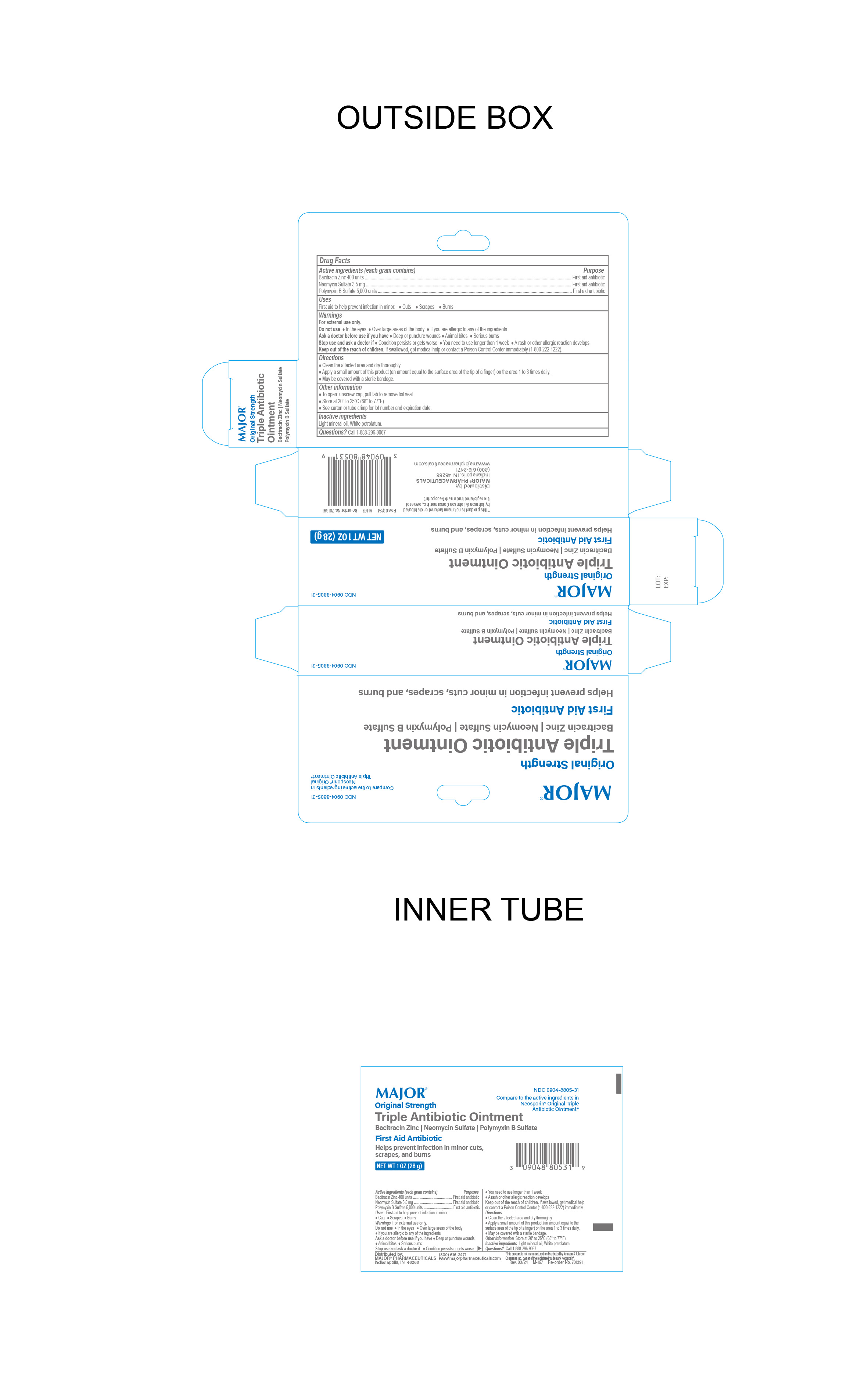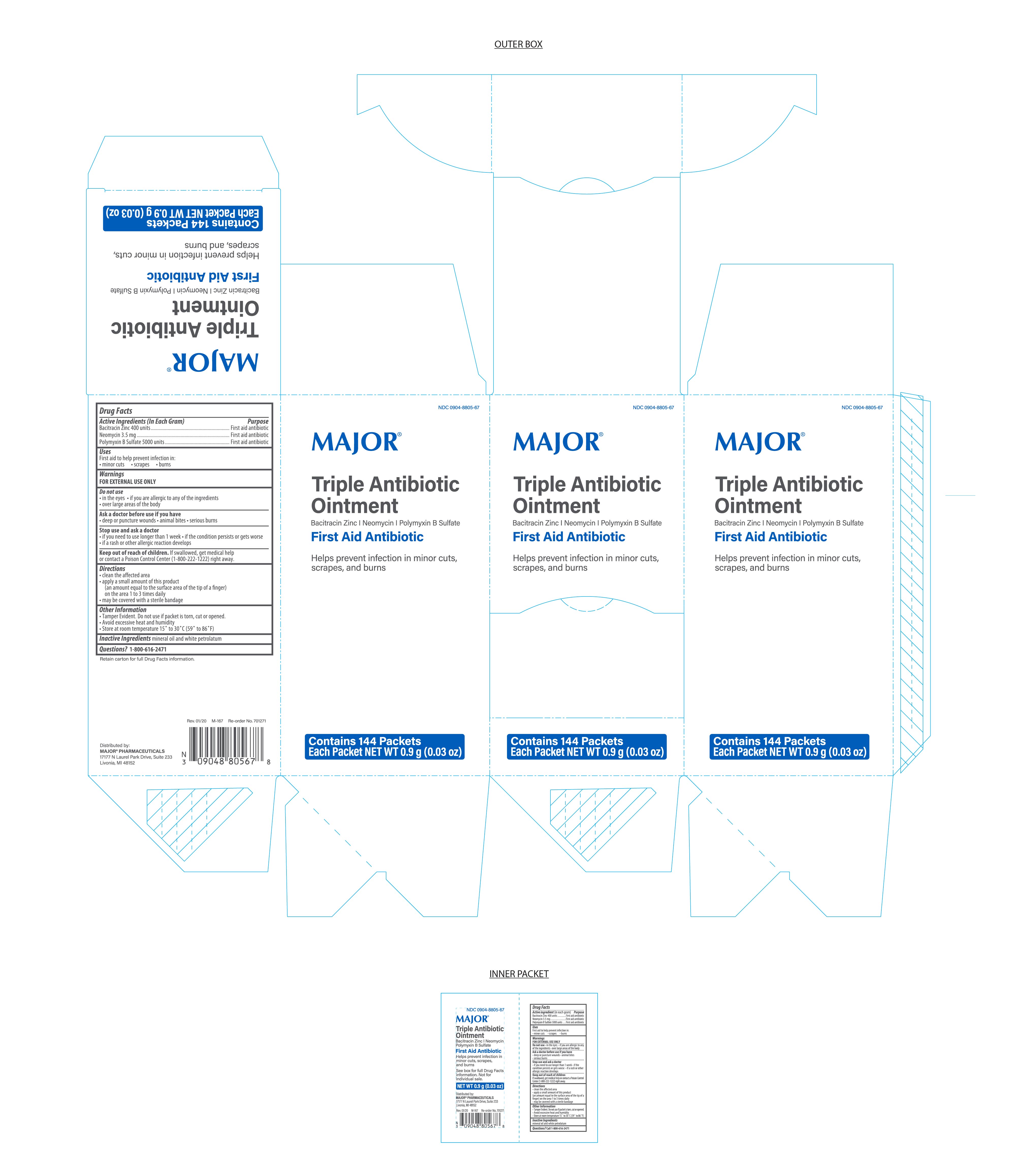 DRUG LABEL: Major Triple Antibiotic
NDC: 0904-8805 | Form: OINTMENT
Manufacturer: Major Pharmaceuticals
Category: otc | Type: HUMAN OTC DRUG LABEL
Date: 20240911

ACTIVE INGREDIENTS: NEOMYCIN SULFATE 3.5 mg/1 g; BACITRACIN ZINC 400 [USP'U]/1 g; POLYMYXIN B SULFATE 5000 [USP'U]/1 g
INACTIVE INGREDIENTS: MINERAL OIL; PETROLATUM

Major Triple Antibiotic Ointment

Active Ingredient

Bacitracin Zinc 400 Units

Purpose

First Aid Antibiotic

Active ingredient

Neomycin 3.5 mg

Purpose

First Aid Antibiotic

Active Ingredient

Polymyxin B Sulfate 5000 Units

Purpose

First Aid Antibiotic

Uses

First Aid to help prevent infection in

- minor cuts
- scrapes
- burns

Warnings

For External Use Only.

Ask Doctor before use if you have

deep or puncture wounds

animal bites

serious burns

Do Not Use

- in eyes
- over large areas of the body
- if you are allergic to any of the ingredients

Stop Use and Ask Doctor if

- If you need to use longer than 1 week
- The condition persists or gets worse
- A rash or allergic reaction develops

Directions

- Clean the affected area
- Apply a small amount of the product (an amount equal to the surface area of the tip of a finger) on the area 1 to 3 times daily
- May be covered with a sterile bandage

Inactive Ingredients

mineral oil and white petrolatum

Questions

Call 1-800-616-2471

Storage Information

Avoid excessive heat and humidity

Store at room temperature 15° to 30°C (59° to 86°F).

Keep out of reach of children

If swallowed, get medical help or contact a Poison Control Center (1-800-222-1222) right away.

Other Information

Tamper evident. Do not use if packet is torn, cut or opened.

Distributed By:

MAJOR® PHARMACEUTICALS

17177 N Laurel Park Drive

Suite 233

Livonia, MI 48152

Product of USA